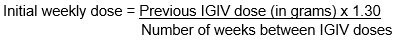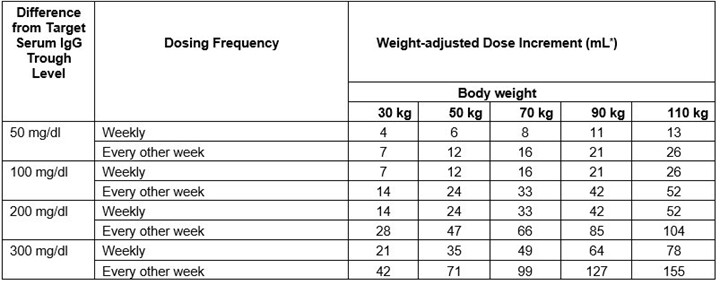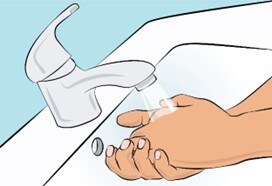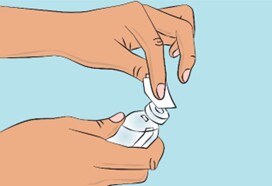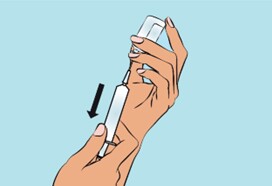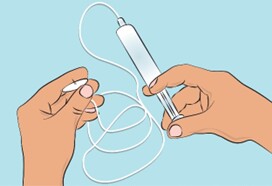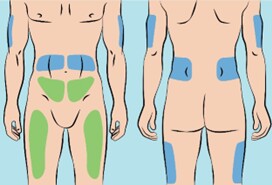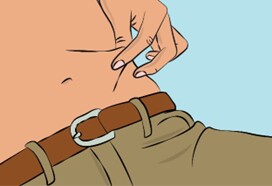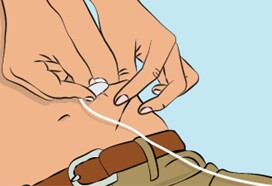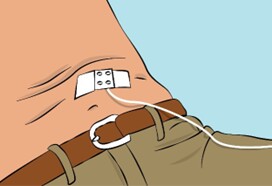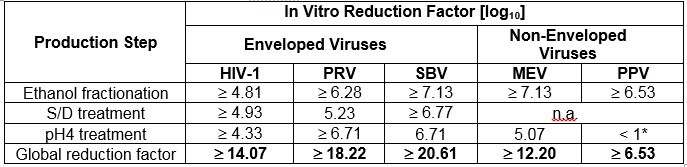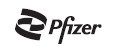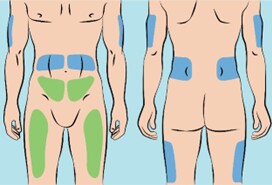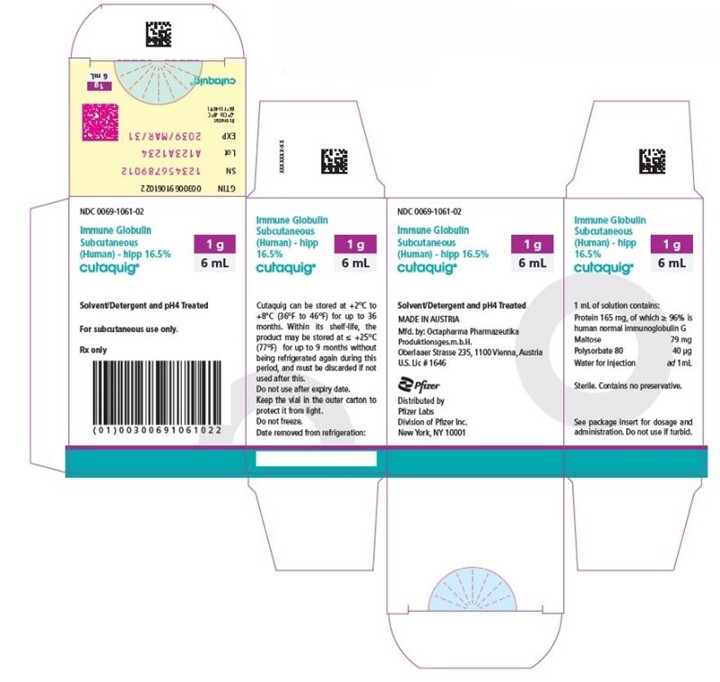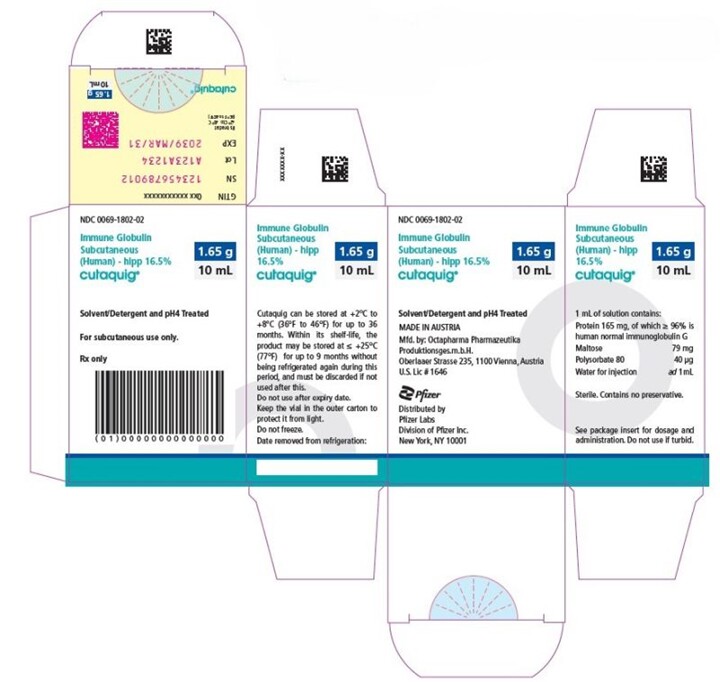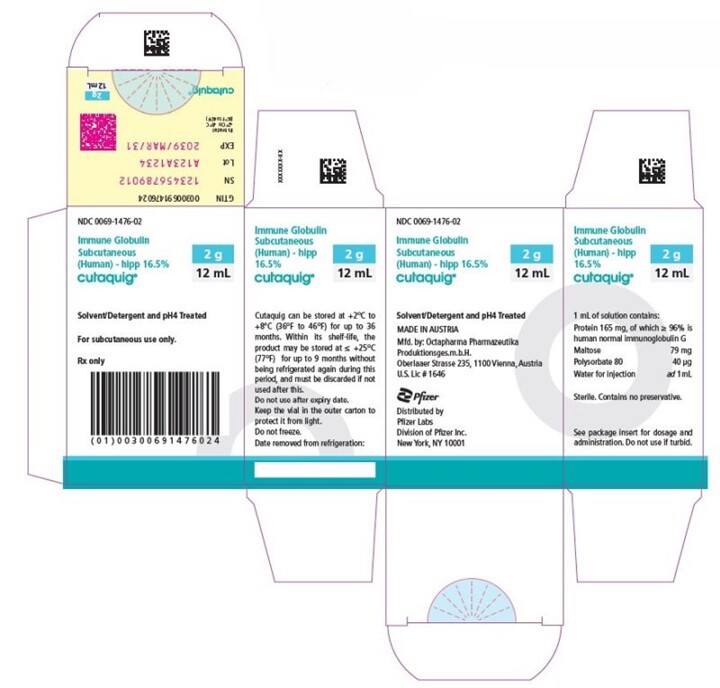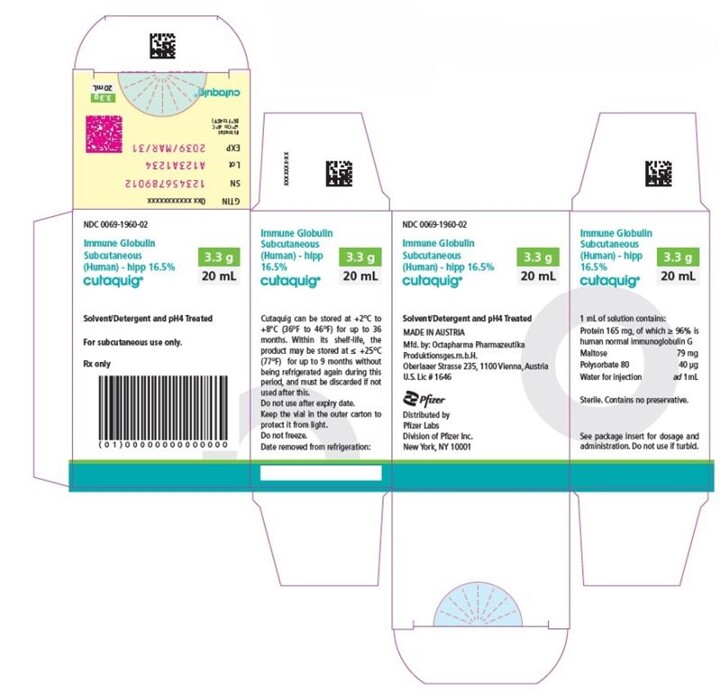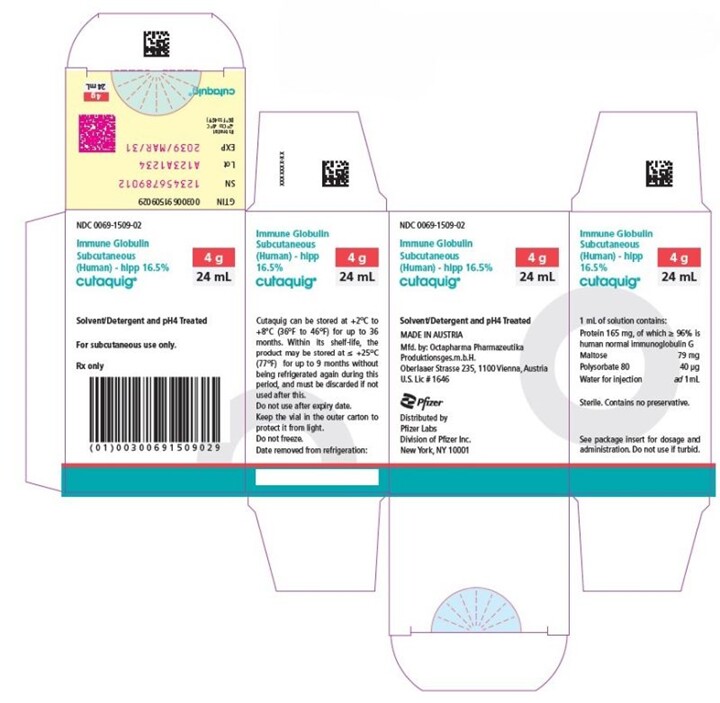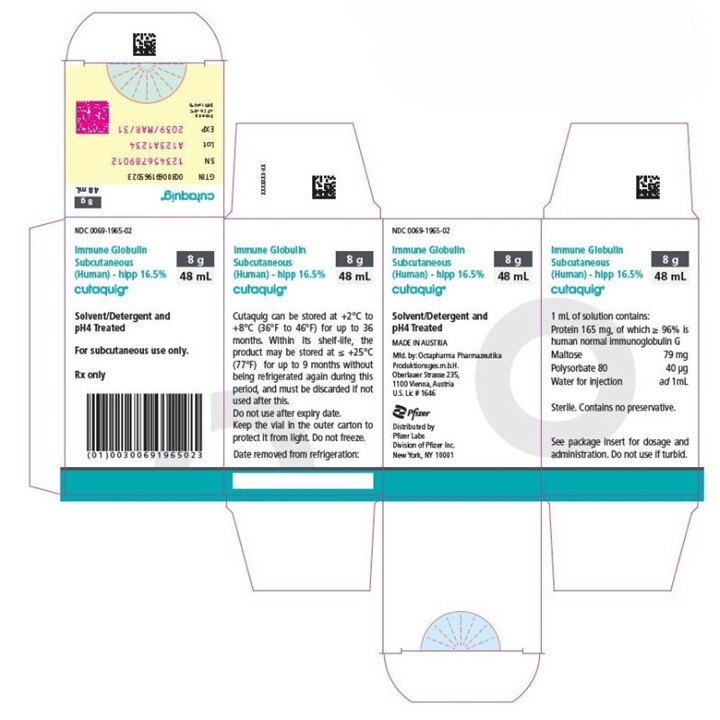 DRUG LABEL: Cutaquig
NDC: 0069-1061 | Form: SOLUTION
Manufacturer: Pfizer Laboratories Div Pfizer Inc
Category: other | Type: PLASMA DERIVATIVE
Date: 20250324

ACTIVE INGREDIENTS: HUMAN IMMUNOGLOBULIN G 165 mg/1 mL

HIGHLIGHTS OF PRESCRIBING INFORMATION

These highlights do not include all the information needed to use CUTAQUIG safely and effectively. See full prescribing information for CUTAQUIG.
CUTAQUIG® (Immune Globulin Subcutaneous (Human) - hipp),
16.5% solution
Initial U.S. Approval: 2018

RECENT MAJOR CHANGES

Indications and Usage (1) 10/2021

Dosage and Administration, Dose (2.1) 10/2021

Dosage and Administration, Administration (2.3) 10/2021

WARNING: THROMBOSIS

See full prescribing information for complete boxed warning

Thrombosis may occur with immune globulin products, including CUTAQUIG. Risk factors may include: advanced age, prolonged immobilization, hypercoagulable conditions, history of venous or arterial thrombosis, use of estrogens, indwelling vascular catheters, hyperviscosity, and cardiovascular risk factors.

For patients at risk of thrombosis, administer CUTAQUIG at the minimum dose and infusion rate practicable. Ensure adequate hydration in patients before administration. Monitor for signs and symptoms of thrombosis and assess blood viscosity in patients at risk of hyperviscosity.

1 INDICATIONS AND USAGE

CUTAQUIG (Immune Globulin Subcutaneous (Human) - hipp) is a 16.5% immune globulin solution for subcutaneous infusion indicated for treatment of primary humoral immunodeficiency (PI) in adults and pediatric patients 2 years of age and older. (1)

2 DOSAGE AND ADMINISTRATION

For subcutaneous use only

Before switching to CUTAQUIG, obtain the patient’s serum IgG trough level to guide subsequent dose adjustments.

Dose (2.1)

Switching from Immune Globulin Intravenous (IGIV) to CUTAQUIG: calculate the dosing by using a dose conversion factor (1.30); Switching from other Immune Globulin Subcutaneous (IGSC): dosing should be the same as for previous IGSC.

Weekly : Start CUTAQUIG one week after last IGIV infusion

Initial weekly dose = Previous IGIV dose (in grams) x 1.30

No. of weeks between IGIV doses

Every other week : Start CUTAQUIG 1 or 2 weeks after the last IGIV dosing or 1 week after the last IGSC administration. Infuse twice the calculated weekly dose.

More frequent than weekly (2-7 times a week): start CUTAQUIG 1 week after last IGIV or IGSC administration. Divide the calculated weekly dose by the desired number of infusions per week.

Adjust dosing according to patient’s pharmacokinetics and clinical response. (see Dose Adjustment)

Administration (2.3):

Administer at regular interval from daily up to every other week. Infusion rate and infusion volume per site may gradually be increased every 2-4 weeks as tolerated by patients.

Infusion sites: up to 6 infusion sites simultaneously, with at least 2 inches between sites. Rotate sites for each administration.

Refer to section 2.3 of full prescribing information for infusion parameters. (2.3)

3 DOSAGE FORMS AND STRENGTHS

CUTAQUIG is a solution containing 16.5% IgG (165 mg/mL) for subcutaneous infusion. (3)

4 CONTRAINDICATIONS

History of anaphylactic or severe systemic reaction to human immune globulin or other components of CUTAQUIG (Polysorbate 80). (4)

IgA deficient patients with antibodies against IgA and a history of hypersensitivity. (4)

5 WARNINGS AND PRECAUTIONS

Hypersensitivity and anaphylactic reactions can occur with CUTAQUIG. IgA-deficient patients with anti-IgA antibodies are at greater risk of severe reactions. (5.1)

Falsely elevated blood glucose readings may occur during and after the infusion of CUTAQUIG with some glucometer and test strip systems. (5.3)

Aseptic meningitis syndrome (AMS) may occur within 2 days of treatment. (5.4)

Monitor patients for signs and symptoms of renal dysfunction. Monitor blood urea nitrogen, serum creatinine, and urine output in patients at risk of acute renal failure. (5.5)

Monitor for clinical signs and symptoms of hemolysis, especially in patients with pre-existing anemia and/or cardiovascular or pulmonary compromise. (5.6)

Monitor for pulmonary adverse reactions (transfusion-related acute lung injury, TRALI). (5.7)

CUTAQUIG is made from human plasma and may carry a risk of transmitting infectious agents, e.g. viruses, the variant Creutzfeldt-Jakob disease (vCJD) agent, and, theoretically, the Creutzfeldt-Jakob disease (CJD) agent. (5.8)

6 ADVERSE REACTIONS

The most common adverse reactions (≥ 5% of study subjects) were local infusion site reactions (such as redness, swelling, itching), headache, fever, dermatitis, asthma, diarrhea, and cough. (6)

To report SUSPECTED ADVERSE REACTIONS, contact Pfizer Inc. at 1-800-438-1985 or FDA at 1-800-FDA-1088 or www.fda.gov/medwatch.

7 DRUG INTERACTIONS

The passive transfer of antibodies may transiently interfere with the immune response to live virus vaccines, such as measles, mumps, varicella and rubella (7.2) and may lead to misinterpretation of the results of serological testing. (7.1)

_________________________________________________________________________________________________________________________

FULL PRESCRIBING INFORMATION

CUTAQUIG (Immune Globulin Subcutaneous (Human) - hipp)

16.5% solution

WARNING: THROMBOSIS

- Thrombosis may occur with immune globulin products, including CUTAQUIG. Risk factors may include: advanced age, prolonged immobilization, hypercoagulable conditions, history of venous or arterial thrombosis, use of estrogens, indwelling central vascular catheters, hyperviscosity, and cardiovascular risk factors. Thrombosis may occur in the absence of known risk factors. [see Warnings and Precautions (5.2), Patient Counseling Information (17) ]

- For patients at risk of thrombosis, administer CUTAQUIG at the minimum dose and infusion rate practicable. Ensure adequate hydration in patients before administration. Monitor for signs and symptoms of thrombosis and assess blood viscosity in patients at risk of hyperviscosity. [see Warnings and Precautions (5.2)]

1 INDICATIONS AND USAGE

CUTAQUIG (Immune Globulin Subcutaneous (Human) - hipp) is a 16.5% immune globulin solution for subcutaneous infusion (IGSC), indicated as replacement therapy for primary humoral immunodeficiency (PI) in adults and pediatric patients 2 years of age and older. This includes, but is not limited to, common variable immunodeficiency (CVID), X-linked agammaglobulinemia, congenital agammaglobulinemia, Wiskott-Aldrich syndrome, and severe combined immunodeficiencies.

2 DOSAGE AND ADMINISTRATION

For subcutaneous use only .

- Before receiving treatment with CUTAQUIG: Obtain the patient's serum Immunoglobulin G (IgG) trough level to guide subsequent dose adjustments (see Dose Adjustment).

2.1 Dose

- Individualize the dose based on the patient’s pharmacokinetic and clinical response. Monitor serum IgG trough levels regularly to guide subsequent dose adjustments as needed (see Dose Adjustment).
- Start CUTAQUIG treatment one week after the last Immune Globulin Intravenous (IGIV)/ Immune Globulin Subcutaneous (IGSC) infusion.

Dose for patients switching to CUTAQUIG from IGIV:

- Establish the initial weekly dose of CUTAQUIG by converting the monthly IGIV dose into an equivalent weekly dose and increasing it using a dose adjustment factor.
- To calculate the initial weekly dose of CUTAQUIG, divide the monthly IGIV dose in grams by the number of weeks between IGIV infusions and then multiply this value with a Dose Adjustment Factor of 1.30.

- To convert the dose (in grams) to milliliters (mL), multiply the calculated dose (in grams) by 6.
- Provided the total weekly dose is maintained, any dosing interval from daily up to weekly can be used and will result in systemic IgG exposure that is comparable to the previous IGIV treatment.
- For every other week dosing, multiply the calculated weekly CUTAQUIG dose by 2.
- For more frequent than weekly dosing (2-7 times a week) divide the calculated weekly CUTAQUIG dose by the desired number of infusions per week (e.g.: if you want to infuse CUTAQUIG 2 times per week, divide the weekly dose by 2).
- On average, serum IgG trough levels were approximately 23% higher during CUTAQUIG administration compared to those obtained during prior IGIV therapy.
- To guide dose adjustments, see Table 1 under Dose Adjustment .

Dose for patients switching to CUTAQUIG from IGSC:

- It is recommended to maintain the same weekly dosing (in grams) of CUTAQUIG that was used for the previous Immune Globulin Subcutaneous (Human) (IGSC) therapy (in grams).
- For every other week dosing, multiply the weekly dose by 2.
- For more frequent than weekly dosing (2-7 times a week) divide the weekly dose by the desired number of infusions per week (e.g.: if you want to infusion CUTAQUIG 2 times per week, divide the weekly dose by 2).
- To convert the dose (in grams) to milliliters (mL), multiply the calculated dose (in grams) by 6.
- Obtain a trough IgG level before switching, monitor clinical response and check the trough IgG level 2 to 3 months after initiating CUTAQUIG.
- To guide dose adjustments, see Table 1 under Dose Adjustment , if the trough IgG level during CUTAQUIG administration differs from the trough IgG level obtained during treatment with the previously administered IGSC product or target trough level.

Dose Adjustment:

Over time the dose may need to be individualized for each patient, depending on the pharmacokinetic and clinical response and on the desired IgG trough level. Measure the patient’s serum IgG trough level 2-3 months after switching to CUTAQUIG or after the last CUTAQUIG dose adjustment, in order to determine if a dose adjustment is necessary.

Calculate the difference between the patient’s target serum IgG trough level (in mg/dL) and the IgG trough level obtained during subcutaneous treatment with CUTAQUIG. Find this difference in column 1 of Table 1 and according to frequency of administration (weekly or every other week) locate the corresponding adjustment amount of CUTAQUIG in mL/administration according to the body weight of the patient.

For more frequent dosing than weekly or every other week, add the weekly increment from Table 1 to the weekly equivalent dose of the patient and then divide by the desired number of administrations per week.

Use the patient’s clinical response as the primary point to consider for any dose adjustment. Additional dose increments may be indicated based on the patient's clinical response (i.e., infection frequency and severity).

Table 1 Incremental adjustment (mL) of weekly or every other week CUTAQUIG dosing based on the calculated difference between actual IgG trough level and the target trough level for the patient*

* Derived from a linear regression model of trough levels and weekly dose per kg body weight.

For example: a patient with body weight of 70 kg is treated weekly and has a trough level of 600 mg/dL, but the target trough level is 900 mg/dL. The difference between the actual trough level (600) and the targeted trough level (900) is plus 300 mg/dL. Therefore, the recommended increase in the weekly dose would be approximately 49 mL.

A patient with a body weight of 50 kg, on an every other week dosing schedule and with an actual trough level of 900 mg/dL has a target trough level of 700 mg/dL. The difference between actual trough level (900) and targeted trough level (700) is minus 200 mg/dL, therefore the patient needs a decrease in his every other week dose of approximately 47 mL.

Monitor the patient’s clinical response and periodically check trough IgG levels, and repeat dose adjustment as needed.

Measles Exposure

If a patient has been exposed to measles, it may be prudent to administer a dose of Immune Globulin Intravenous as soon as possible and within 6 days of exposure. A dose of 400 mg/kg should provide a serum level > 240 mIU/mL of measles antibodies for at least two weeks.

If a patient is at risk of future measles exposure and receives a dose of less than 245 mg/kg subcutaneously per week, increase the dose to 245 mg/kg.

2.2 Preparation

CUTAQUIG is a clear and colorless solution that may turn to slightly opalescent and pale yellow during storage. Do not use the solution if it appears cloudy or contains particulates.

- Use aseptic technique when preparing and administering CUTAQUIG.
- Prior to administration visually inspect each vial of CUTAQUIG for particulate matter, whenever the solution and container permit.
- Do not mix CUTAQUIG with other products.
- Do not dilute CUTAQUIG.
- Do not shake the solution.
- Check the labeling for the expiration date and do not use beyond this date.
- CUTAQUIG vials are for single use only. Discard any unused product after each infusion in accordance with local requirements.
- Do not freeze. Do not use frozen product.
- Record lot number in patient’s medical history.

2.3 Administration

CUTAQUIG is for subcutaneous use only.

Administer CUTAQUIG by a healthcare provider, or by caregiver or self-administered by the patient after appropriate training.

Infuse CUTAQUIG in the following areas: abdomen, thigh, upper arm, and/or upper leg/hip area.

CUTAQUIG is intended for subcutaneous use using an infusion pump and compatible syringe(s).

Infuse CUTAQUIG simultaneously into up to 6 different sites. Infusion sites should be at least 2 inches (5 cm) apart. Rotate infusion sites between subsequent administrations.

Volume:

For patients not already on IGSC therapy, do not exceed the maximum initial volume per injection site of 25 mL/site for adults (≥17 years), 15 mL/site (for ages 7-16 years) and 10 mL/site (for ages 2-6 years) for the first 2 infusions.

For subsequent infusions, if tolerated, you may gradually increase infusion volume/site by approximately 10 mL per infusion site in adults (≥17 years) and by approximately 5-10 mL per infusion site in children (2-16 years) every 2-4 weeks.

The maximum infusion volume is 40 mL/site (for adults ≥17 years), 29 mL/site (for ages 7-16 years) and 15.5 mL/site (for ages 2-6 years).

Rate:

For patients not already on IGSC therapy, do not exceed the maximum recommended flow rates per hour per infusion site of 20 mL per hour per site for adults (≥17 years) and 15 mL per hour per site for children (2-16 years) for the first 2 infusions.

For subsequent infusions, if tolerated, you may gradually increase the infusion rate by approximately 10mL/hr/site in adults (≥17 years) and by approximately 5-10 mL/hr/site in children (2-16 years) every 2-4 weeks.

The maximum infusion rate is 52 mL per hour per site for adults (≥17 years) and 25 mL per hour per site for children (2-16 years).

Table 2 Infusion Volumes and Infusion Rates (Infusion rate and infusion volume per site may gradually be increased every 2-4 weeks as tolerated by patients)

Infusion parameters* |  | Infusion Number
 |  | First 2 infusions | Subsequent infusions
Volume (mL/site) | Adults ≥17 years | ≤ 25 | gradually increase by approximately 10 mL/site every 2-4 weeks up to a maximum of 40
 | 7-16 years | ≤ 15 | gradually increase by approximately 5-10 mL/site every 2-4 weeks up to a maximum of 29
 | 2-6 years | ≤ 10 | gradually increase by approximately 5-10 mL/site every 2-4 weeks up to a maximum of 15.5
Rate (mL/hr/site) | Adults ≥17 years | ≤ 20 | gradually increase by approximately 10 mL/hr/site every 2-4 weeks up to a maximum of 52
 | 2-16 years | ≤ 15 | gradually increase by approximately 10 mL/hr/site every 2-4 weeks up to a maximum of 25

* As tolerated

Administration/Handling instructions

CUTAQUIG is for subcutaneous use only.

Follow the administration guidance below and use aseptic technique when administrating CUTAQUIG.

Figure 1

1. Getting ready for infusion
- Choose and prepare a clean work area.
- Gather your infusion equipment:
Infusion pump and compatible syringe(s).
Needle or needleless transfer device (for drawing up product from the vial).
Infusion set (varies according to manufacturer’s instructions).
Infusion tubing and Y-connector (if required).
Ancillary supplies: disinfectant wipes, gauze or transparent dressing, tape and sharps container.
Patient’s treatment diary/log book.
- Wash your hands thoroughly and let them dry (Figure 1).

Figure 2

2. Checking and opening the vials
- If taken out of the refrigerator, allow products to reach room temperature (≤ 25°C / 77°F).
- Inspect each vial carefully:
Check that labelled dose is correct and based on prescription.
Check that the expiration date has not been passed.
Check the appearance of the solution: do not use the solution if it is cloudy or contains particles.
Make sure the protective cap is not broken or missing.
- Remove the protective cap.
- Disinfect the rubber stopper by using a sterile wipe and allow it to dry (Figure 2).

Figure 3

3. Preparing and filling the syringe
- Open sterile syringe and needle or needleless transfer device.
- If a needleless transfer device is used, follow the instructions of the device manufacturer.
- If the transfer is done using needle and syringe follow the instructions below:
Attach the needle to the syringe with a screw action.
Draw back on the plunger to fill the syringe with air which should be roughly equal to the amount of solution needed from the vial.
Insert the needle into the center of the vial stopper and turn the vial upside down. To avoid foaming, ensure that the tip of the needle is not in the solution, and then inject the air.
Next, move the needle so that the tip is in the solution, and then slowly draw up the desired volume of CUTAQUIG (Figure 3).
Withdraw the needle from the vial.
This procedure might be repeated if you need to use more than one vial.
When finished, remove the needle and dispose of it into the sharps bin and proceed to the next step.

Figure 4

4. Preparing the infusion pump and tubing
- Follow the manufacturer’s instructions for preparing the infusion pump.
- Prime the administration tubing according to manufacturer’s instruction to eliminate all remaining air (Figure 4).
- Stop priming before fluid reaches the needle tip.

Figure 5

5. Preparing the infusion site(s) and inserting the infusion needle(s)
- CUTAQUIG can be infused in the following areas: abdomen, thigh, upper arm, and/or upper leg/hip area (Figure 5).
- The number and location of injection sites depends on the volume of the total dose. The infusion sites should be at least 2 inches apart. A maximum of 6 infusion sites can be used simultaneously.
- Rotate sites between infusions.
- Avoid inserting the needle into scars, tattoos or injured/inflamed skin areas and inspect skin for signs of infection.
- Clean your skin at your selected infusion site(s) with an antiseptic skin wipe starting at the center and working outward in a circular motion, and allow each site to dry before proceeding.

Figure 6

- Pinch the skin between your thumb and foreﬁnger around the injection site (Figure 6) and insert the needle into the subcutaneous tissue (Figure 7). The angle of the needle will depend on the type of infusion set being used.

Figure 7

Figure 8

- Secure the needle in place by applying sterile gauze and tape or transparent dressing (Figure 8).

6. Checking the infusion

- Check needle placement by pulling back on the syringe plunger. There should not be any blood return in the tubing.

- If blood return is seen, remove needle and restart from step 5 with new tubing at a different location.

7. Starting the infusion

- Start the infusion. Follow infusion pump manufacturer’s instructions.

8. Recording the infusion

- On each vial of CUTAQUIG, you will find a peel-off portion of the label with the batch number details. Stick this label in your patient’s treatment diary or infusion log book. Record details of the dose, date, time, infusion site location and any infections, side effects or other comments.

9. After infusion is complete

- Gently remove the needle(s) and immediately place into the sharps bin.

- If necessary, press a small piece of gauze on the needle site and apply a dressing.

- Discard all used disposable supplies as well as any unused product and the empty vial(s) as recommended by your healthcare provider and according to local requirements.

- Clean and store the infusion pump according to the manufacturer’s instructions.

For self-administration, provide the patient and caregiver with instructions and appropriate training for infusion at home or other appropriate setting. Verify that the patient or caregiver is capable of self-administration or administration, respectively, using appropriate technique.

3 DOSAGE FORMS AND STRENGTHS

CUTAQUIG is a solution containing 16.5% IgG (165 mg/mL).

4 CONTRAINDICATIONS

CUTAQUIG is contraindicated:

- In patients who have had an anaphylactic or severe systemic reaction to the subcutaneous administration of human immune globulin or to any of the components of CUTAQUIG such as Polysorbate 80.
- In IgA-deficient patients with antibodies against IgA and a history of hypersensitivity to human globulin treatment.

5 WARNINGS AND PRECAUTIONS

5.1 Hypersensitivity

Severe hypersensitivity reactions may occur with CUTAQUIG, even in patients who tolerated previous treatment with human immune globulin. If a hypersensitivity reaction occurs, discontinue the CUTAQUIG infusion immediately and initiate appropriate treatment. Have epinephrine immediately available to treat any severe acute hypersensitivity reaction.

IgA-deficient patients with known anti-IgA antibodies have a higher risk of developing potentially severe hypersensitivity and/or anaphylactic reactions (including anaphylaxis and shock) with administration of CUTAQUIG. CUTAQUIG contains on average 0.206 mg of IgA /mL.

5.2 Thrombosis

Thrombosis may occur following treatment with immune globulin products, including CUTAQUIG. Risk factors may include: advanced age, prolonged immobilization, hypercoagulable conditions, history of venous or arterial thrombosis, use of estrogens, indwelling central vascular catheters, hyperviscosity, and cardiovascular risk factors. Thrombosis may occur in absence of known risk factors.

Consider baseline assessment of blood viscosity in patients at risk for hyperviscosity, such as those with cryoglobulins, fasting chylomicronemia/markedly high triglycerides, or monoclonal gammopathies. For patients at risk of thrombosis, administer CUTAQUIG at the minimum dose and infusion rate practicable. Ensure adequate hydration in patients before administration. Monitor for signs and symptoms of thrombosis and assess blood viscosity in patients at risk for hyperviscosity. [see WARNING , Patient Counseling Information (17)]

5.3 Falsely Elevated Glucose Readings

Blood Glucose Testing: Some types of blood glucose testing systems (for example, those based on the glucose dehydrogenase pyrroloquinolinequinone (GDH-PQQ) or glucose-dye-oxidoreductase methods) falsely interpret the maltose contained in CUTAQUIG as glucose. This may potentially result in falsely elevated glucose readings and, consequently, in the inappropriate administration of insulin, resulting in life-threatening hypoglycemia. Also, cases of true hypoglycemia may go untreated if the hypoglycemic state is masked by falsely elevated glucose readings. Accordingly, when administering CUTAQUIG, measure blood glucose with a glucose-specific method. The product information of the blood glucose testing system, including that of the test strips, should be carefully reviewed to determine if the system is appropriate for use with maltose-containing parenteral products. If any uncertainty exists, contact the manufacturer of the testing system to determine if the system is appropriate for use with maltose-containing parenteral products.

5.4 Aseptic Meningitis Syndrome (AMS)

Aseptic Meningitis Syndrome can occur with CUTAQUIG. AMS has been reported after the use of human immune globulin administered intravenously and subcutaneously. It usually begins a few hours to 2 days following treatment and occurs more frequently in females than in males.

AMS is characterized by the following signs and symptoms: severe headache, nuchal rigidity, drowsiness, fever, photophobia, painful eye movements, nausea and vomiting. Cerebrospinal fluid (CSF) studies frequently show pleocytosis up to several thousand cells per mm ^3 , predominantly from the granulocytic series, and elevated protein levels up to several hundred milligram/dL, but negative culture results. To rule out other causes of meningitis, conduct a thorough neurological examination on patients showing such symptoms and signs, including CSF studies. Discontinuation of immunoglobulin treatment has resulted in remission of AMS within several days without sequelae.

5.5 Renal Dysfunction/Failure

Acute renal dysfunction/failure, acute tubular necrosis, proximal tubular nephropathy, osmotic nephrosis and death may occur with use of human immune globulin, especially those containing sucrose. CUTAQUIG does not contain sucrose. Ensure that patients are not volume-depleted before administration of CUTAQUIG.

In patients at risk of developing renal dysfunction because of any degree of preexisting renal insufficiency or predisposition to acute renal failure (such as diabetes mellitus, age greater than 65 years, volume depletion, sepsis, paraproteinemia, or patients receiving known nephrotoxic drugs) monitor renal function and consider lower, more frequent dosing [see Dosage and Administration (2), Patient Counseling Information (17)].

Periodic monitoring of renal function and urine output is particularly important in patients judged to have a potential increased risk of developing acute renal failure. Assess renal function, including measurements of blood urea nitrogen (BUN) and serum creatinine, before the initial infusion of CUTAQUIG and again at appropriate intervals thereafter. If renal function deteriorates, consider discontinuing CUTAQUIG.

5.6 Hemolysis

IgG products, including CUTAQUIG, can contain blood group antibodies that may act as hemolysins and induce in vivo coating of red blood cells (RBCs) with immunoglobulin, causing a positive direct antiglobulin (Coombs’) test result. Delayed hemolytic anemia can develop subsequent to immune globulin therapy due to enhanced RBC sequestration, and acute hemolysis, consistent with intravascular hemolysis, has been reported.

Monitor CUTAQUIG recipients for clinical signs and symptoms of hemolysis, particularly patients with risk factors (such as non-O blood group, administration of high IgG doses (≥ 2g/kg BW)). Underlying inflammatory state in a patient may increase the risk of hemolysis but its role is uncertain. Consider appropriate confirmatory laboratory testing if signs and symptoms of hemolysis are present after CUTAQUIG infusion.

5.7 Transfusion-related Acute Lung Injury (TRALI)

Non-cardiogenic pulmonary edema may occur in patients administered human immune globulin products. TRALI is characterized by severe respiratory distress, pulmonary edema, hypoxemia, normal left ventricular function, and fever. Typically, it occurs within 1 to 6 hours following transfusion.

Monitor patients for pulmonary adverse reactions. If TRALI is suspected, perform appropriate tests for the presence of anti-neutrophil antibodies in both the product and patient’s serum. Patients with TRALI may be managed using oxygen therapy with adequate ventilatory support.

5.8 Transmittable Infectious Agents

Because CUTAQUIG is made from human plasma, it may carry a risk of transmitting infectious agents, e.g., viruses, the variant Creutzfeldt-Jakob disease (vCJD) agent and, theoretically, the Creutzfeldt-Jakob disease (CJD) agent. This also applies to unknown or emerging viruses and other pathogens. No cases of transmission of viral diseases or CJD have been associated with the use of CUTAQUIG. All infections suspected by a physician to have possibly been transmitted by CUTAQUIG should be reported to Pfizer Inc. at 1-800-438-1985.

5.9 Interference with Laboratory Tests

After infusion of CUTAQUIG, the transitory rise of the various passively transferred antibodies in the patient’s blood may yield false positive serological test results, with the potential for misleading interpretation. Passive transmission of antibodies to erythrocyte antigens (e.g.. A, B, and D) may cause a positive direct or indirect antiglobulin (Coombs’) test.

6 ADVERSE REACTIONS

The most common adverse reactions (AR) observed in ≥ 5% of study subjects were local infusion site adverse reactions (such as redness, swelling, and itching), headache, fever, dermatitis, asthma, diarrhea, and cough.

6.1 Clinical Trials Experience

Because clinical trials are conducted under widely varying conditions, adverse reaction rates observed in the clinical trials of a drug cannot be directly compared to rates in the clinical trials of another drug and may not reflect the rates observed in practice.

Clinical safety data are based on one pivotal open-label, single arm, prospective, multicenter major effectiveness study of CUTAQUIG in subjects with primary humoral immunodeficiency (PI), previously treated with Immune Globulin Intravenous (Human) (IGIV) for at least 6 months and its extension study. The pivotal study was conducted in Europe and North America and was followed by an extension safety study (prospective, open-label, single-arm, multicenter phase 3). 21 patients were initially treated in the pivotal study and 6 patients from Canada were newly treated. Total number of patients in both studies combined was 81.

In the pivotal study, the 75 subjects in the Safety Analysis Set received 4462 infusions, with a mean of 59 infusions administered per subject. The average dose of CUTAQUIG used per subject was 0.187 g/kg in adult subjects, 0.150 g/kg in young children, 0.164 g/kg in older children and 0.170 g/kg in adolescents.

In the extension study, the 27 subjects in the Safety Analysis Set received 2777 infusions. The average dose of CUTAQUIG used per subject was 0.166 g/kg in adult subjects, 0.127 g/kg in young children, 0.210 g/kg in older children and 0.160 g/kg in adolescents.

Excluding infections, a total of 74 out of 81 subjects (91%) experienced 1527 adverse reactions (ARs, defined as adverse events occurring during or within 72 hours of infusion or any adverse events otherwise causally related) in both studies. Of the 1527 ARs 1088 were infusion site reactions. The proportion of infusions with adverse reactions was 0.21. Sixty-one subjects (75%) had at least one systemic AR.

Local reactions were the most common ARs and were experienced by 59 subjects (73%). The rate of infusion site reaction per infusion was 0.15. Most local ARs were either mild (transient AR causing discomfort but not interfering with routine activities [87.5%]) or moderate (AR sufficiently discomforting to interfere with routine activities [10.3%]) in intensity.

Table 3 and Table 4 summarize adverse reactions occurring in ≥ 5% of adult subjects and pediatric subjects in both the pivotal and the extension study.

Table 3 Adverse reactions* in ≥ 5% of adult subjects and rate per infusion in adult subjects (pivotal and extension study)

ARs | Number (%) of subjects (N=43) | Number (rate**) of ARs (N=3956 infusions)
Local reaction | 31 (72.1) | 648 (16.4)
Systemic ARs
Headache | 8 (18.6) | 10 (0.002)
Dermatitis | 5 (11.6) | 6 (0.001)
Fever | 5 (11.6) | 5 (0.001)
Diarrhoea | 5 (11.6) | 7 (0.002)
Muscle spasms | 4 (9.3) | 5 (0.001)
Back pain | 4 (9.3) | 4 (0.001)
Arthralgia | 3 (7.0) | 3 (0.001)

* Excluding infections.

** Rate = total number of adverse reactions divided by total number of infusions.

Table 4 Adverse reactions* in ≥ 5% pediatric subjects and rate per infusion in pediatric subjects (pivotal and extension study)

ARs | Number (%) of subjects (N=38) | Number (rate**) of ARs (N=3283 infusions)
Local reaction | 28 (73.7) | 442 (13.5)
Systemic ARs
Asthma | 4 (10.5) | 7 (0.002)
Cough | 4 (10.5) | 5 (0.002)
Vomiting | 4 (10.5) | 5 (0.002)
Nasal congestion | 3 (7.9) | 4 (0.001)
Fever | 3 (7.9) | 4 (0.001)
Headache | 3 (7.9) | 3 (0.001)
Alanine aminotransferase increased | 3 (7.9) | 3 (0.001)
Leukopenia | 3 (7.9) | 3 (0.001)
Neutropenia | 3 (7.9) | 3 (0.001)
Dermatitis | 2 (5.3) | 3 (0.001)
Oropharyngeal pain | 2 (5.3) | 3 (0.001)
Urticaria | 2 (5.3) | 2 (0.001)
Aspartate aminotransferase increased | 2 (5.3) | 2 (0.001)
Abdominal pain | 2 (5.3) | 2 (0.001)
Ear pain | 2 (5.3) | 2 (0.001)

* Excluding infections.

** Rate = total number of adverse reactions divided by total number of infusions.

The most frequent infusion site reactions were redness, swelling, and itching. During the pivotal study period the incidence of local reactions decreased over time from 37% of infusions triggering an infusion site reaction during the first 4 infusions to around 16% of infusions with an infusion site reaction during the last 4 infusions.

6.2 Postmarketing Experience

The following adverse reactions have been identified during post-approval use of immune globulin products administered subcutaneously. Because these reactions are reported voluntarily from a population of uncertain size, it is not always possible to reliably estimate their frequency or establish a causal relationship to drug exposure.

Table 5 summarizes adverse reactions that have been reported during post-marketing use of immune globulin products:

Table 5 Adverse reactions reported during post-marketing use of immune globulin products

MedDRA System Organ Class (SOC) | Adverse reactions
Blood and lymphatic system disorders | Pancytopenia, leukopenia, hemolytic anemia
Immune system disorders | Anaphylactic reaction, hypersensitivity reaction, allergic reaction, angioneurotic edema, face edema
Psychiatric disorders | Agitation
Nervous system disorders | Loss of consciousness, cerebrovascular accident, aseptic meningitis, seizures, migraine, tremor, paresthesia, dizziness
Cardiac disorders | Cardiac arrest, tachycardia, palpitations
Vascular disorders | Thromboembolism, thrombosis, circulatory collapse, hypertension, hematoma
Respiratory, thoracic and mediastinal disorders | Transfusion-related acute lung injury, acute respiratory distress syndrome, respiratory failure, pulmonary embolism, apnea, cyanosis, hypoxia, pulmonary edema, bronchospasm, dyspnea, cough, wheezing
Gastrointestinal disorders | Hepatic function abnormal, nausea, vomiting, abdominal distension, abdominal pain upper
Skin and subcutaneous tissue disorders | Stevens-Johnson syndrome, epidermolysis, erythema multiforme, eczema, urticaria, rash (erythematous), alopecia, skin discoloration, skin mass, skin reaction, skin/infusion site ulceration, skin/infusion site necrosis
Musculoskeletal and connective tissue disorders | Back pain, arthralgia, pain in extremity, myalgia
Renal and urinary disorders | (Acute) renal failure
General disorders and administration site condition | Chills, chest pain, chest discomfort, hot flush, flushing, hyperhidrosis, fatigue, influenza-like illness, malaise
Investigations | Hepatic enzyme increased, coombs test positive, free hemoglobin present, hemoglobin increased, haptoglobin decreased

The following adverse reactions have been identified during post-approval use of CUTAQUIG: dizziness, nausea, pruritus and fatigue. Because these reactions are reported voluntarily from a population of uncertain size, it is not always possible to reliably estimate their frequency or establish a causal relationship to drug exposure.

To report SUSPECTED ADVERSE REACTIONS, contact Octapharma USA Inc. at 1-866-766-4860 or FDA at 1-800-FDA-1088 or www.fda.gov/medwatch.

7 DRUG INTERACTIONS

7.1 Serological Testing

Various passively transferred antibodies in immunoglobulin preparations may lead to misinterpretation of results of serological testing.

7.2 Live Virus Vaccines

The passive transfer of antibodies with immunoglobulin administration may interfere with the response to live virus vaccines such as measles, mumps, rubella, and varicella. Inform the immunizing medical practitioner of recent therapy with CUTAQUIG so that appropriate precautions can be taken. [See Patient Counselling Information (17)]

8 USE IN SPECIFIC POPULATIONS

8.1 Pregnancy

Risk Summary

No human data are available to indicate the presence or absence of drug-associated risk. Animal reproduction studies have not been conducted with CUTAQUIG. It is not known whether CUTAQUIG can cause fetal harm when administered to a pregnant woman or can affect reproduction capacity. Immune globulins cross the placenta from maternal circulation increasingly after 30 weeks of gestation. In the U.S. general population, the estimated background risk of major birth defects and miscarriage in clinically recognized pregnancies is 2-4% and 15-20%, respectively.

8.2 Lactation

Risk summary

No human data are available to indicate the presence or absence of drug associated risk. The developmental and health benefits of breastfeeding should be considered along with the mother’s clinical need for CUTAQUIG and any potential adverse effects on the breastfed infant from CUTAQUIG or from the underlying maternal condition.

8.4 Pediatric Use

The safety and efficacy of CUTAQUIG have been established for primary humoral immunodeficiency in the pediatric age group 2 to 16 years CUTAQUIG was evaluated in 38 pediatric subjects with primary humoral immunodeficiency (26 children and 12 adolescents) in the pivotal and extension studies. [see Clinical Studies (14)]

Overall safety and efficacy findings in pediatric age group were comparable to those seen in adults. However, infusion site reactions were more commonly observed in adults compared to the pediatric population.

PK parameters are comparable between pediatric and adult patients. No pediatric-specific dose requirements were necessary to achieve the desired serum IgG levels.

Safety and effectiveness of CUTAQUIG in pediatric patients below the age of 2 have not been established.

8.5 Geriatric Use

Clinical studies of CUTAQUIG did not include sufficient numbers of subjects aged 65 and over to determine whether they respond differently from younger subjects. Three study subjects enrolled in the clinical trial were 65 years and over. In general, dose selection for an elderly patient should be cautious. Medical practitioners should start at the low end of the dosing range to reduce the risk of hyperviscosity and precipitation of cardiac, renal, or hepatic adverse reaction and of concomitant disease or other drug therapy.

11 DESCRIPTION

CUTAQUIG (Immune Globulin Subcutaneous (Human) - hipp), is a solvent/detergent (S/D)-treated, sterile preparation of highly purified immunoglobulin G (IgG) derived from large pools of human plasma. CUTAQUIG is a solution for injection to be administered subcutaneously.

This preparation contains approximately 165 mg of protein per mL (16.5%), of which not less than 96% is normal human immunoglobulin G. CUTAQUIG contains not more than 3% aggregates, not less than 94% monomers and dimers, and not more than 3% fragments. The product contains on average 0.206 mg of IgA /mL.

The sodium content of the final solution is not more than 30 mmol/L and the pH is between 5.0 and 5.5. The osmolality is 310 - 380 mOsmol/kg.

The manufacturing process for CUTAQUIG isolates IgG without additional chemical or enzymatic modification, and the Fc portion is maintained intact. CUTAQUIG contains the IgG antibody activities present in the donor population. IgG subclasses are fully represented with the following approximate percent of total IgG: IgG1 is 70%, IgG2 is 25%, IgG3 is 3% and IgG4 is 2%.

CUTAQUIG contains a broad spectrum of IgG antibodies against bacterial and viral agents that are capable of opsonization and neutralization of microbes and toxins. It contains maltose (79 mg/mL), but no preservatives or sucrose.

All units of human plasma used in the manufacture of CUTAQUIG are provided by FDA-approved blood and plasma establishments, and are tested by FDA-licensed serological tests for HBsAg, antibodies to HCV and HIV and Nucleic Acid Test (NAT) for HCV and HIV-1 and found to be non-reactive (negative).

The product is manufactured by the cold ethanol fractionation process followed by ultrafiltration and chromatography. The manufacturing process includes treatment with an organic S/D mixture composed of tri-n-butyl phosphate (TNBP) and Octoxynol. The CUTAQUIG manufacturing process shows significant viral reduction in in vitro studies (Table 6). These reductions are achieved through a combination of process steps including cold ethanol fractionation, S/D treatment and pH 4 treatment.

Table 6 Pathogen Reduction During CUTAQUIG Manufacturing

* Not calculated for global Log 10 Reduction Factor

HIV-1: Human Immunodeficiency Virus - 1

PRV: Pseudorabies Virus, model virus for e.g. Hepatitis B Virus (HBV)

SBV: Sindbis Virus, model virus for Hepatitis C Virus (HCV)

MEV: Mouse Encephalomyelitis Virus, model virus for Human Parvovirus B19

PPV: Porcine Parvovirus, model virus for Hepatitis A Virus (HAV)

n.a.: not applicable

12 CLINICAL PHARMACOLOGY

12.1 Mechanism of Action

CUTAQUIG supplies a broad spectrum of opsonizing and neutralizing Immunoglobulin G (IgG) antibodies against a wide variety of bacterial and viral agents. It has a distribution of immune globulin subclasses closely proportional to that in native human plasma. The mechanism of action in primary humoral immunodeficiency (PI) has not been fully elucidated; however adequate doses may restore abnormally low immune globulin G levels to the normal range and thus help in preventing infections.

12.2 Pharmacodynamics

CUTAQUIG contains mainly IgG with a broad spectrum of antibodies against various infectious agents reflecting the IgG activity found in the donor population. CUTAQUIG which is prepared from pooled material from not less than 1000 donors, has an IgG subclass distribution similar to that of native human plasma. Adequate doses of Immune Globulin Subcutaneous (Human) (IGSC) can restore an abnormally low IgG level to the normal range. Standard pharmacodynamic studies were not performed.

12.3 Pharmacokinetics

A pharmacokinetic (PK) sub-study was conducted in 37 subjects (18 adults and 19 pediatric subjects) who were enrolled in the pivotal safety and efficacy study. Blood samples for PK study were collected prior to switching to CUTAQUIG (IGIV profile: PK IV), after the 11 th infusion of CUTAQUIG (first SC profile: PK SC1) and after the 28th infusion of CUTAQUIG (second SC profile: PK SC2). The objective of the PK sub-study was to compare the AUCs following the IV and SC administration. At steady state, the ratio of geometric least square means (SC2:IV) was 1.06, (90% CI: 1.03, 1.10), indicating comparable exposure between IGSC and IGIV treatment (standardized to a 7-day period). The actual dose converting factor was 1.41 (1.21, 1.89). Using a Population PK model calculation, the DCF was determined in a statistically more advanced manner at 1.33 for a median patient.

Serum IgG and IgG subclass trough levels were nearly constant during the IGSC phase of the study, with higher mean levels after SC treatment compared with those following IGIV. At the end of the IGIV period, trough levels ranged from 5.0 g/L to 15.1 g/L. Over the entire IGSC treatment period individual trough levels of total IgG ranged between 4.4 g/L to 24.0 g/L.

Table 7 summarizes the Key PK parameters for CUTAQUIG. PK parameters are comparable between pediatric and adult patients.

Table 7 Key Pharmacokinetic Parameters for CUTAQUIG and IGIV

Parameter [Arithmetic Mean (SD)] | IGIV (N=37) | CUTAQUIG (N=37)
C max [g/L] | 18.01 (4.5) | 13.47 (3.7)
C min [g/L] | 10.09 (2.5) | 11.66 (2.9)
T max [h] # | 3.38 (1.6 – 69.5) | 49.62 (0.8 – 98.3)
AUC tau [g*hr/L] | 2013 (570)* | 2233 (586)
AUC tau [mg*day/dL] | 8389 (2376)* | 9302 (2441)
CL ^+ (mL/day/kg) | 1.5 (0.5) | 1.9 (0.6)
Actual IgG Dose per kg Body Weight and Week (g/kg/week) | 0.121 (0.049) | 0.170 (0.066)

# T max is presented as Median (range)

* standardized to a 7-day period

^+ apparent clearance (CL/F) for CUTAQUIG (F = bioavailability)

Compared with weekly administration, administration of CUTAQUIG on a every other week basis at double the weekly dose is expected to result in comparable IgG exposure [equivalent AUCs, with a slightly higher IgG peak (Cmax) and slightly lower trough (Cmin)] in both adult and pediatric subjects. In addition, for the same total weekly dose, CUTAQUIG infusions given 2, 3, 5, or 7 times per week (frequent dosing) are expected to produce IgG exposures comparable to weekly dosing in both adult and pediatric subjects.

13 NONCLINICAL TOXICOLOGY

13.1 Carcinogenesis, Mutagenesis, Impairment of Fertility

No animal studies were conducted with CUTAQUIG to assess carcinogenesis, mutagenesis or impairment of fertility.

13.2 Animal Toxicology and/or Pharmacology

Safety of CUTAQUIG has been demonstrated in several standard nonclinical toxicology studies (local tolerance in rabbits, cardiovascular and respiratory effects in dogs, thrombogenic potential in rabbits).

The product given subcutaneously to CD1 mice inoculated with Streptococcus pneumoniae showed a dose related improvement in survival.

TNBP and Octoxynol may be found in CUTAQUIG in trace amounts. In animals and in vitro studies, these compounds were not genotoxic and did not have mutagenic properties. They did not show teratogenic effects when administered to pregnant rabbits and rats during organogenesis.

14 CLINICAL STUDIES

There were 2 clinical studies, one was a pivotal, prospective, open-label, single-arm, multicenter study to evaluate the pharmacokinetics (PK), efficacy, tolerability and safety of subcutaneous human immunoglobulin (CUTAQUIG) in subjects with primary humoral immunodeficiency (PI). The other was an extension study.

The pivotal study was conducted in 75 subjects (37 adult and 38 pediatric subjects < 17 years of age) who received weekly SC infusions with CUTAQUIG during a 12-week wash-in/wash-out period followed by a 12-month efficacy period during which efficacy, pharmacokinetics, safety, tolerability, and quality of life (QoL) parameters of CUTAQUIG were evaluated. All patients received study treatment and 68 patients completed the study. Seven patients (4 adolescents and 3 adults) were withdrawn prematurely. Reasons for withdrawal from the study were patient’s decision in 6 cases and patient’s noncompliance in one adolescent patient.

During the efficacy period the mean weekly dose was 174 mg/kg BW, with individual doses ranging from 60 to 390 mg/kg BW. The median duration of infusion per week was 1.5 hours.

All enrolled subjects (n=75) were included in the Safety Analysis Set and the Full Analysis Set (FAS). Four subjects were excluded from the Per-Protocol (PP) Set because they terminated early before the start of the primary treatment period.

Overall, 36 female subjects and 39 male subjects participated in this study. The youngest subject enrolled in the study was 2 years old and the oldest was 73 years old. The mean age in the adult group (17–75 yrs) was 47.5 years. The mean age at time of enrollment in the pediatric groups was 4.2 years, 7.9 years and 14.1 years in the 3 pediatric age groups [young children (ages 2-5 years), older children (ages 6-11 years) and adolescents (ages 12-16 years)] respectively. Reported race was white for all but one subject, and all subjects were of not Hispanic/Latino ethnicity.

The main objective of the pivotal study was to assess the efficacy of CUTAQUIG in preventing serious bacterial infections (SBI defined as bacteremia/sepsis, bacterial meningitis, osteomyelitis/septic arthritis, bacterial pneumonia and visceral abscess). This endpoint was considered successful if the upper bound of the one-sided 99% confidence interval for the rate of SBIs was < 1.0 per subject-year of follow up. This criterion was met, as no SBIs were reported at any time during the study.

Other endpoints of the pivotal study included, but were not limited to: the number of episodes of any other infections, along with type and severity of infection and time to resolution; number of days of use and annual rate of antibiotics; absence and number of days of absence from work/school/ kindergarten/day care; and hospitalizations due to infections and number of days and annual rate of hospitalisation.

Efficacy results of the pivotal study are summarized in Table 8 .

Table 8 Summary of efficacy results of the pivotal study (FAS).

 | Adults | Pediatrics | Total
Number of subjects (efficacy period) | 37 | 38 | 75
Total number of subject years Infections Annual rate [number of SBIs* per subject-year (upper one-sided 99% CI)] Annual rate [number of other infections per subject-year (two-sided 95% CI)] | 35.5 0 (0.13) # 3.4 (2.2, 5.4) | 35.0 0 (0.13) # 3.1 (2.0, 4.8) | 70.5 0 (0.06) # 3.3 (2.4, 4.5)
Systemic antibiotic use Number of subjects (%) Annual rate [days on treatment per subject-year (two-sided 95%CI)] | 25 (67.6%) 32.1 (17.2, 60.1) | 24 (63.2%) 62.6 (31.0, 126.4) | 49 (65.3%) 47.2 (28.4, 78.6)
Days out of work/school/kindergarten/day care due to infections Number of days Annual rate [days per subject-year (two-sided 95% CI)] | 72 2.0 (0.7, 5.7) | 180 5.2 (2.8, 9.4) | 252 3.6 (2.1, 6.0)
Hospitalization due to infections Number of days Annual rate [days per subject-year (two-sided 95% CI)] | 0 0 0 (0.1) # | 4 29 0.8 (0.3, 2.6) | 4 29 0.4 (0.1, 1.3)

* Defined as bacterial pneumonia, bacteremia/septicemia, osteomyelitis/septic arthritis, bacterial meningitis, and visceral abscess.

CI = confidence interval

# calculation for the upper limit of two-sided 95% or one-sided 99% CI was based on standard Poisson model for zero counts

The extension study was a prospective, open-label, single-arm, multicenter phase 3 safety study that enrolled 27 patients (17 adults, 10 patients aged <17 years) with PI. Twenty-one patients were initially treated in the pivotal study and 6 patients were newly enrolled. Mean age was 39 years (range 6 to 73 years). Ten patients (37%) were male, all but 2 were White, none was Hispanic or Latino.

Patients received CUTAQUIG on a weekly (25 patients) or an “every other week” schedule (2 patients). The primary objective of this study was to assess the medium-to-long term safety and tolerability of CUTAQUIG. Secondary efficacy assessments included occurrence of SBIs, the annual rate of all infections of any kind or seriousness, hospitalizations due to infections, and antibiotic use. One adult had bacteremia/sepsis. The rate of SBI per person-year was 0.03 for adults, and 0.0 for all other age groups (overall rate of 0.018). Secondary efficacy results are summarized in Table 9 .

Table 9 Summary of efficacy results of the extension study (FAS)

 | Adults | Pediatrics | Total
Number of subjects | 17 | 10 | 27
Total number of subject years Infections Annual rate [number of SBIs* per subject year (upper limit of one-sided 99% CI)] Annual rate [number of other infections per subject-year (two-sided 95% CI)] | 33.4 0.03 (0.31) 2.3 (1.0, 4.9) | 20.7 0 (0.22) # 2.0 (0.9, 4.8) | 54.1 0.02 (0.19) 2.2 (1.2, 3.9)
Systemic antibiotic use Number of subjects (%) Annual rate [treatment days per subject-year (two-sided 95% CI)] | 13 (76.5%) 30.9 (12.2, 78.4) | 6 (60.0%) 70.6 (22.7, 220.0) | 19 (70.4%) 46.0 (21.3, 99.4)
Days out of work/school/kindergarten/day care due to infections Number of days Annual rate [days per subject-year (two-sided 95% CI)] | 55 1.7 (0.4 to 6.5) | 75 3.6 (1.3 to 10.3) | 130 2.4 (1.0, 5.5)
Hospitalization due to infections Number of days Annual rate [days per subject-year (two-sided 95% CI)] | 3 10 0.3 (0.07 to 1.3) | 0 0 0 (0.2) # | 3 10 0.2 (0.04, 0.8)

* Defined as bacterial pneumonia, bacteremia/septicemia, osteomyelitis/septic arthritis, bacterial meningitis, and visceral abscess.

CI = confidence interval

# calculation for the upper limit of two-sided 95% or one-sided 99% CI was based on standard Poisson model for zero counts

16 HOW SUPPLIED/STORAGE AND HANDLING

CUTAQUIG is supplied in 1 g, 1.65 g, 2 g, 3.3 g, 4 g or 8 g single-use vials.

Carton NDC Number | Container NDC Number | Size | Grams Protein
0069-1061-02 0069-1802-02 0069-1476-02 0069-1960-02 0069-1509-02 0069-1965-02 | 0069-1061-01 0069-1802-01 0069-1476-01 0069-1960-01 0069-1509-01 0069-1965-01 | 6 mL 10 mL 12 mL 20 mL 24 mL 48 mL | 1 1.65 2 3.3 4 8

- Components used in the packaging of CUTAQUIG are not made with natural rubber latex.
- Store at +2°C to +8°C (36°F to 46°F) for up to 36 months from the date of manufacture. Within its shelf-life, the product may be stored at room temperature up to +25°C (77°F) for up to 9 months without being refrigerated again during this period, and must be discarded if not used after this.
- Keep the vial in the outer carton to protect it from light.
- Check the product expiration date on the vial label. Do not use beyond the expiration date.
- Do not freeze. Do not use frozen product.
- Do not mix with other products.
- Do not shake the vial.
- Use aseptic technique when preparing and administering CUTAQUIG. Prior to administration, visually inspect each vial for particulate matter, whenever the solution and container permit. Do not use if the solution is cloudy or contains particulates.
- The vial is for single-use only. Discard any unused product after each infusion, in accordance with local requirements.

17 PATIENT COUNSELING INFORMATION

Advise the patients to read the FDA-approved patient labeling (Patient Information and Instructions for Use).

Inform patients to immediately report the following signs and symptoms to their healthcare provider:

- Hypersensitivity reactions to CUTAQUIG (including hives, generalized hives, tightness of the chest, wheezing, low blood pressure, and anaphylaxis): Advise patients to have epinephrine immediately available to treat any acute severe hypersensitivity reaction and ensure patients and their caregivers are properly trained in its use. [see Warnings and Precautions (5.1)].
- Pain and/or swelling of an arm or leg with warmth over the affected area, discoloration of an arm or leg, unexplained shortness of breath, chest pain or discomfort that worsens on deep breathing, unexplained rapid pulse, or numbness or weakness on one side of the body [see Warnings and Precautions (5.2)].
- Severe headache, neck stiffness, drowsiness, fever, sensitivity to light, painful eye movements, nausea, and vomiting [see Warnings and Precautions (5.4)].
- Decreased urine output, sudden weight gain, fluid retention/edema, and/or shortness of breath [see Warnings and Precautions (5.5)].
- Fatigue, increased heart rate, yellowing of the skin or eyes, and dark-colored urine [see Warnings and Precautions (5.6)].
- Severe breathing problems, lightheadedness, drops in blood pressure, and fever [see Warnings and Precautions (5.7)].

Inform patients to be tested periodically to make sure they have the appropriate levels of IgG in their blood. These tests may result in adjustments to the CUTAQUIG dose.

Inform patients/caregivers that because CUTAQUIG is made from human blood, it may carry a risk of transmitting infectious agents, e.g., viruses, the variant Creutzfeldt-Jakob disease (vCJD) agent and, theoretically, the Creutzfeldt-Jakob disease (CJD) agent [see Warnings and Precautions (5.8), Description (11)].

Inform patients that CUTAQUIG may interfere with the response to live virus vaccines (e.g., measles, mumps, rubella, and varicella) and to notify their immunizing physician of recent therapy with CUTAQUIG [see Drug Interactions (7.2)].

Home treatment/Self administration

- If self-administration is deemed appropriate by the physician, it is highly important to clearly instruct the patient/caregiver and to provide a thorough training on subcutaneous administration of CUTAQUIG. The patient/caregiver needs to demonstrate the ability to independently administer subcutaneous infusions and document it.
- Ensure the patient/caregiver understands the importance of regular subcutaneous infusions to maintain appropriate steady state IgG levels.
- Instruct the patient/caregiver to keep a treatment diary/log where all information about each infusion should be clearly documented.
- Inform patients to interrupt or terminate the CUTAQUIG infusion if a hypersensitivity reaction occurs.
- Inform patients that they should be tested regularly to make sure they have the correct levels of CUTAQUIG (IgG) in their blood. These tests may result in adjustment to the CUTAQUIG dose.
- Instruct the patient/caregiver that local injection site reactions (such as swelling, redness, itching) are a common side effect of subcutaneous treatment, but also tell them to contact their healthcare provider if local reactions increase in severity or persist for more than a few days.
- Inform the patient that injection sites should be rotated between infusions and that CUTAQUIG is for subcutaneous infusion only.

Manufactured by:

Octapharma Pharmazeutika Produktionsges.m.b.H.

Oberlaaer Strasse 235

1100 Vienna, Austria

U.S. License No. 1646

Distributed by:

Pfizer Labs

Division of Pfizer Inc.

New York, NY 10001

PATIENT PACKAGE INSERT

Patient Information

CUTAQUIG

(kew' ta kwig)

Immune Globulin Subcutaneous (Human) - hipp, 16.5% solution

Information for Patients

The following summarizes important information about CUTAQUIG. Please read it carefully before using CUTAQUIG and each time you get a refill, as there may be new information. This Patient Information does not take the place of talking with your healthcare provider about your medical condition or your treatment. If you have any questions after reading this, ask your healthcare provider.

What is CUTAQUIG?

CUTAQUIG is a ready-to-use liquid solution of Immunoglobulin G (IgG), also called antibodies, which protect the body against infection. CUTAQUIG is used to treat patients with primary humoral immunodeficiency (PI).

There are many forms of PI. The most common types of PI result in an inability to make a very important type of protein called antibodies, which help the body fight off infections from bacteria or viruses. Regular administration of CUTAQUIG will help your body to fight bacteria and viruses that cause infections. CUTAQUIG is made from human plasma that is donated by healthy people. CUTAQUIG contains antibodies collected from these healthy people; these antibodies replace the missing antibodies in PI patients.

Who should NOT use CUTAQUIG?

Do not use CUTAQUIG if you have ever had a severe allergic reaction to immune globulin or other blood products.

Tell your healthcare provider if you:

- ever had any severe reaction to other immune globulin medicines.
- were told that you have a condition called IgA deficiency.
- have a history of heart or blood vessel disease.
- have had blood clots or “thick blood”.
- have been immobile for some time.

What should I tell my healthcare provider before using CUTAQUIG?

Talk to your healthcare provider about any medical conditions that you have or have had.

Tell your healthcare provider that you are taking CUTAQUIG before you get vaccination as vaccines may not work while you are taking CUTAQUIG.

Tell your healthcare provider about all of the prescription and non-prescription medicines you take, including over-the-counter medicines, dietary supplements, or herbal medicines.

Tell your healthcare provider if you are pregnant or plan to get pregnant, or if you are nursing because CUTAQUIG might not be right for you.

Tell your healthcare provider if you have diabetes. If you need to do glucose testing, your healthcare provider may tell you to use a different way to monitor your blood sugar levels on the day that you receive a CUTAQUIG infusion. Some types of blood glucose testing systems (so called glucometers) falsely interpret the maltose contained in CUTAQUIG as glucose. If you are uncertain ask your healthcare provider which glucose testing system you can use while using CUTAQUIG.

How should I use CUTAQUIG?

CUTAQUIG is given under the skin (subcutaneously). This type of infusion can be given at home by yourself or by your caretaker after appropriate training. Administration of CUTAQUIG should be done at regular intervals. Only use CUTAQUIG by yourself after you have been instructed by your healthcare provider.

What are the possible or reasonably likely side effects of CUTAQUIG?

The most common side effects of CUTAQUIG are:

- Infusion site reactions (including but not limited to redness, swelling, itching, fluid in tissue, pain, mass, bruising)
- Headache
- Elevated body temperature

Call your healthcare provider or emergency department immediately if you have any of the following symptoms: difficulty breathing, chest tightness, itching, swelling of the face, rash, hives or dizziness. These could be signs of a serious allergic reaction.

Tell your healthcare provider immediately if you have any of the following symptoms. They could be signs of a serious drug reaction:

- Decreased urination, sudden weight gain, or swelling in the legs. These could be signs of a kidney problem.
- Bad headache with nausea, vomiting, stiff neck, fever, and sensitivity to light. These could be signs of meningitis, which is irritation of the lining around your brain.
- Pain, swelling, warmth, discoloration of an arm or leg, unexplained shortness of breath, chest pain, discomfort that worsens on deep breathing, unexplained rapid pulse, a lump in your legs or arms, or numbness or weakness on one side of the body. These could be signs of a blood clot.
- Chest pain or trouble breathing, or blue lips or extremities. These could be signs of a serious heart or blood problem.
- Brown or red urine, fast heart rate, yellow skin or eyes. These could be signs of a liver or heart problem.
- Fever over 100°F (38°C). This could be sign of an infection.

These are not all of the possible side effects from CUTAQUIG. Ask your healthcare provider for more information. You are encouraged to report side effects to Pfizer Inc. at 1-800-438-1985 or FDA at 1-800-FDA-1088.

Talk to your healthcare provider about any side effect that bothers you or that does not go away. You can ask your healthcare provider for more information on possible side effects.

Whenever giving yourself treatments at home, make sure another responsible person is present to help treat side effects or help if a serious adverse reaction occurs. Ask your healthcare provider whether you should have rescue medications, such as antihistamines or epinephrine. If prescribed epinephrine for severe allergic reactions, make sure you receive adequate training from a healthcare provider for its proper use.

How should I store CUTAQUIG?

Keep CUTAQUIG in the outer carton to protect it from exposure to light.

Do not freeze CUTAQUIG.

Store CUTAQUIG at 36°F- 46°F (+2°C to +8°C) for up to 36 months from the date of manufacture. Within its shelf-life, the product can be stored at room temperature up to 77°F (up to +25°C) for up to 9 months without being refrigerated again during this period, and must be discarded if not used after this.

Do not use CUTAQUIG after the expiration date printed on the vial.

Dispose all materials, including any unused CUTAQUIG, in an appropriate container.

What else should I know about CUTAQUIG?

Do not use CUTAQUIG for a medical condition for which it was not prescribed. Do not share CUTAQUIG with other people, even if they have the same diagnosis and symptoms that you have.

Manufactured by

Octapharma Pharmazeutika Produktionsges.m.b.H.

Oberlaaer Strasse 235

1100 Vienna, Austria

U.S. License No. 1646

Distributed by

Pfizer Labs

Division of Pfizer Inc.

New York, NY 10001

CUTAQUIG ® is a registered trademark of Octapharma.

Patient Instructions for Use

CUTAQUIG

Immune Globulin Subcutaneous (Human) - hipp, 16.5% solution

Detailed patient handling instructions for administration of CUTAQUIG

CUTAQUIG is for subcutaneous use only.

Use CUTAQUIG only after you have been properly instructed and trained by your healthcare provider.

Follow the administration guidance below step by step and use aseptic/sterile technique when administrating CUTAQUIG. Use gloves if you have been told to do so when preparing the infusion.

1. Prepare the necessary number of CUTAQUIG vials
- If stored in the refrigerator, put the vials at room temperature at least 90 minutes prior to infusion.
- Do not heat the vials or put them into the microwave.
- Do not shake the vials to avoid foaming.

Figure 1

2. Getting ready for infusion
- Choose and prepare a clean work area using antiseptic wipes or disinfecting solution.
- Gather your infusion equipment:
- Infusion pump and compatible syringe(s)
Needle or needleless transfer device (for drawing up product from the vial)
Infusion set (varies according to manufacturer’s instructions)
Infusion tubing and Y-connector (if required)
Ancillary supplies: disinfectant wipes, gauze or transparent dressing, tape and sharps container
Treatment diary and pen
- Wash and clean your hands thoroughly and let them dry as has been shown to you during the training (Figure 1). You can wear gloves during the preparation of the infusion if you have been told so during the training.
- If necessary, program the pump according to the user manual and as you have been shown during the training by your healthcare provider.

Figure 2

3. Checking and opening the vials
- Allow products to reach room temperature (77°F / ≤ 25°C).
- Inspect each vial carefully:
Check that the labelled dose is correct and based on your prescription.
Check that the expiration date has not been passed.
Check the appearance of the solution (it should be clear and colorless to pale yellow or slightly opalescent).
Do not use the solution if it is cloudy or contains particles.
Make sure the protective cap is not broken or missing.
- Remove the protective cap.
- Disinfect the rubber stopper by using a sterile wipe and allow it to dry (Figure 2).

Figure 3

4. Preparing and filling the syringe
- Open sterile syringe and needle or needleless transfer device.
- If a needleless transfer device is used, follow the instructions of the device manufacturer.
- If the transfer is done using needle and syringe, follow the instructions below:
Attach the needle to the syringe with a screw action.
Draw back on the plunger to fill the syringe with air. The amount of air should be roughly equal to the amount of solution needed from the vial.
Insert the needle into the center of the vial stopper and slowly turn the vial upside down. To avoid foaming, ensure that the tip of the needle is not in the solution; then inject air by pushing the plunger of the syringe.
Next, move the needle so that the tip is in the solution; then slowly draw up the desired volume of CUTAQUIG solution, making sure that the needle tip is always in the solution (Figure 3).
Withdraw the needle from the vial.
This procedure might be repeated if you need multiple vials for the calculated dose.
When finished, remove the needle and dispose of it into the sharps bin.
Once finished, proceed to the next step.

Figure 4

5. Preparing the infusion pump and tubing
- Follow the manufacturer’s instructions for preparing the infusion pump.
- To prime the administration tubing, attach the filled syringe to the infusion tubing and gently push the plunger to fill the tubing with CUTAQUIG, as has been shown to you during training (Figure 4).
- Stop priming before fluid reaches the needle tip.

Figure 5

6. Preparing infusion site(s) and inserting the infusion needle(s)
- CUTAQUIG can be infused into the following areas: abdomen, thigh, upper arm, and/or upper leg/hip area (Figure 5).
- The number and location of injection sites depends on the volume of the total dose.
- The infusion sites should be at least 2 inches apart. Do not use more than 6 infusion sites at the same time.
- Rotate sites between infusions.
- Avoid inserting the needle into scars, tattoos, stretch marks or any skin that has signs of infection (such as injured/inflamed/red skin area).
- Clean your skin at your selected infusion site(s) with an antiseptic skin wipe, starting at the center and working outward in a circular motion. Allow each site to dry before proceeding.

Figure 6

- Pinch the skin between your thumb and foreﬁnger around the injection site (Figure 6). Carefully remove the needle cover and insert the needle into the skin (Figure 7). The angle of the needle will depend on the type of infusion set being used.
- Put transparent dressing or sterile tape and gauze over the administration site to keep the needle in place during the infusion.

Figure 7

Figure 8

7. Checking the infusion
- Check needle placement by pulling back on the syringe plunger. There should not be any blood return in the tubing (Figure 8).
- If blood return is seen, remove the needle and restart from step 6 with new tubing at a different location.

8. Starting the infusion

- Start the infusion. Follow infusion pump manufacturer’s instructions.

9. Recording the infusion

- On each vial of CUTAQUIG, you will find a peel-off portion of the label with the batch number details. Stick this label in your patient’s treatment diary or infusion log book. Record details of the dose, date, time, infusion site location and any infections, side effects or other comments in connection with this infusion.

10. After infusion is complete

- Gently remove the dressing and the needle(s) and immediately place into the sharps bin.

- Press a small piece of gauze on the needle site and apply a dressing.

- Discard all used disposable supplies as well as any unused product and the empty vial(s) as recommended by your healthcare provider and according to local requirements.

- Tidy up and securely store all the reusable equipment (e.g., pump) until the next infusion.

If you encounter any problems or experience side effects during or after the infusion, contact your healthcare provider. When doing so, keep your treatment diary or log book with you to be able to give all necessary information.

You can also report side effects to the FDA at 1-800-FDA-1088 or online under www.fda.gov/medwatch.

Manufactured by

Octapharma Pharmazeutika Produktionsges.m.b.H.

Oberlaaer Strasse 235

1100 Vienna, Austria

U.S. License No. 1646

Distributed by

Pfizer Labs

Division of Pfizer Inc.

New York, NY 10001

CUTAQUIG ® is a registered trademark of Octapharma.

Issued 03 2025.

PACKAGE LABEL - PRINCIPAL DISPLAY PANEL

Immune Globulin Subcutaneous (Human) - hipp, 16.5%

Cutaquig

6 mL

NDC 0069-1061-02

Cutaquig

10 mL

NDC 0069-1802-02

Cutaquig

12 mL

NDC 0069-1476-02

Cutaquig

20 mL

NDC 0069-1960-02

Cutaquig

24 mL

NDC 0069-1509-02

Cutaquig

48 mL

NDC 0069-1965-02